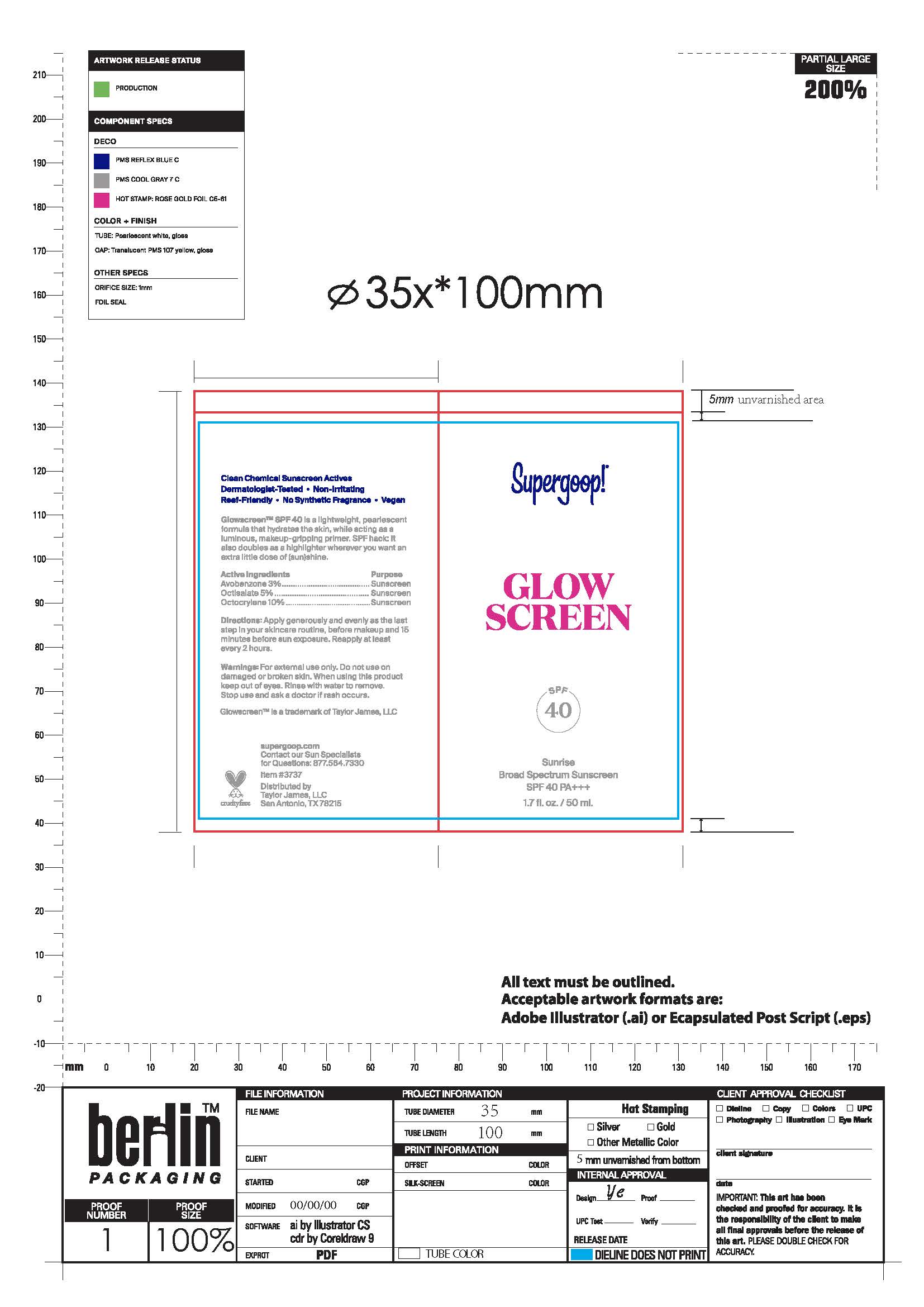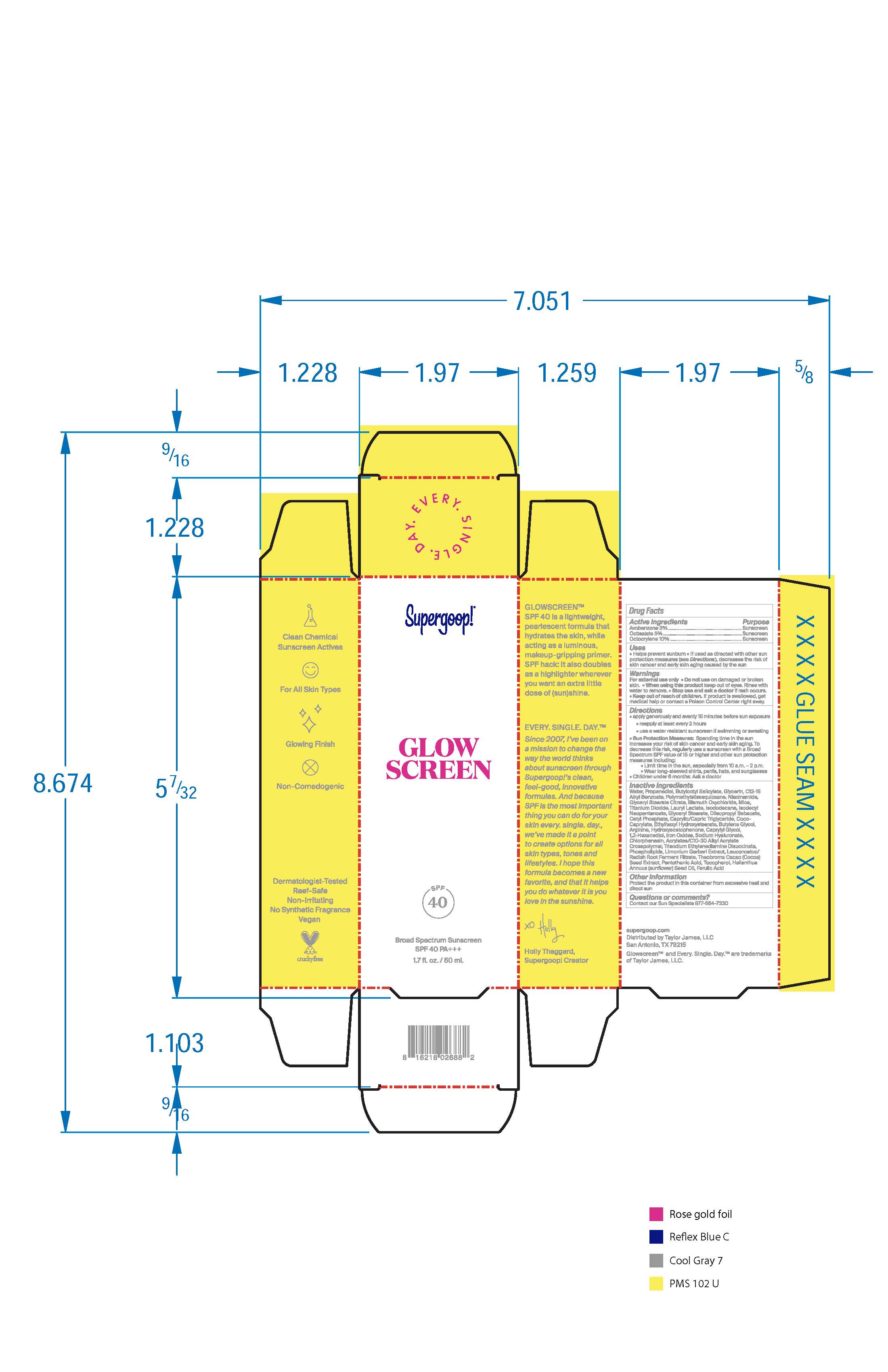 DRUG LABEL: Glow Screen SPF 40
NDC: 75936-216 | Form: CREAM
Manufacturer: Supergoop, LLC
Category: otc | Type: HUMAN OTC DRUG LABEL
Date: 20241204

ACTIVE INGREDIENTS: AVOBENZONE 3 g/100 mL; OCTISALATE 5 g/100 mL; OCTOCRYLENE 10 g/100 mL
INACTIVE INGREDIENTS: WATER; PROPANEDIOL; BUTYLOCTYL SALICYLATE; GLYCERIN; ALKYL (C12-15) BENZOATE; POLYMETHYLSILSESQUIOXANE (4.5 MICRONS); NIACINAMIDE; GLYCERYL STEARATE CITRATE; BISMUTH OXYCHLORIDE; MICA; TITANIUM DIOXIDE; LAURYL LACTATE; ISODODECANE; ISODECYL NEOPENTANOATE; GLYCERYL MONOSTEARATE; DIISOPROPYL SEBACATE; CETYL PHOSPHATE; MEDIUM-CHAIN TRIGLYCERIDES; COCO-CAPRYLATE; ETHYLHEXYL HYDROXYSTEARATE; BUTYLENE GLYCOL; ARGININE; HYDROXYACETOPHENONE; CAPRYLYL GLYCOL; 1,2-HEXANEDIOL; FERRIC OXIDE RED; HYALURONATE SODIUM; CHLORPHENESIN; CARBOMER INTERPOLYMER TYPE A (ALLYL SUCROSE CROSSLINKED); TRISODIUM ETHYLENEDIAMINE DISUCCINATE; LECITHIN, SOYBEAN; LIMONIUM GERBERI WHOLE; LEUCONOSTOC/RADISH ROOT FERMENT FILTRATE; COCOA; PANTOTHENIC ACID; TOCOPHEROL; SUNFLOWER OIL; FERULIC ACID

Glow Screen SPF 40

Active Ingredients Purpose
Avobenzone 3% Sunscreen
Octisalate 5% Sunscreen
Octocylene 10% Sunscreen

Uses
Helps prevent sunburn.

If used as directed with other sun protection measures (see Directions), decreases the risk of skin cancer and early skin aging caused by the sun

Keep out of reach of children. If product is swallowed, get medical help or contact a Poison Control Center right away.

Stop use and ask a doctor if rash occurs.

Warnings
For external use only

Do not use on damaged or broken skin.

When using this product keep out of eyes. Rinse with water to remove.

Directions

- Apply generously and evenly 15 minutes before sun exposure

- Reapply at least every 2 hours

Use a water resistant sunscreen if swimming or sweating
Sun Protection Measures: Spending time in the sun increases your risk of skin cancer and early skin aging. To decrease this risk, regularly use a sunscreen with a Broad Spectrum SPF value of 15 or higher and other sun protection measures including:
Limit time in the sun, especially from 10a.m. – 2p.m.

- Wear long-sleeved shirts, pants, hats, and sunglasses

- Children under 6 months: Ask a doctor

Inactive Ingredients
Water, Propanediol, Butyloctyl Salicylate, Glycerin, C12-15 Alkyl Benzoate, Polymethylsilsesquioxane, Niacinamide, Glyceryl Stearate Citrate, Bismuth Oxychloride, Mica, Titanium Dioxide, Lauryl Lactate, Isododecane, Isodecyl Neopentanoate, Glyceryl Stearate, Diisopropyl Sebacate, Cetyl Phosphate, Caprylic/Capric Triglyceride, Coco-Caprylate, Ethylhexyl Hydroxystearate, Butylene Glycol, Arginine, Hydroxyacetophenone, Caprylyl Glycol, 1,2-Hexanediol, Iron Oxides, Sodium Hyaluronate, Chlorphenesin, Acrylates/C10-30 Alkyl Acrylate Crosspolymer, Trisodium Ethylenediamine Disuccinate, Phospholipids, Limonium Gerberi Extract, Leuconostoc/Radish Root Ferment Filtrate, Theobroma Cacao (Cocoa) Seed Extract, Pantothenic Acid, Tocopherol, Helianthus Annuus (sunflower) Seed Oil, Ferulic Acid

PACKAGE LABEL

Supergoop!

Glowscreen

SPF 40 Sunrise

Broad Spectrum Sunscreen

SPF 40 PA+++

1.7 fl. oz./ 50 ml.